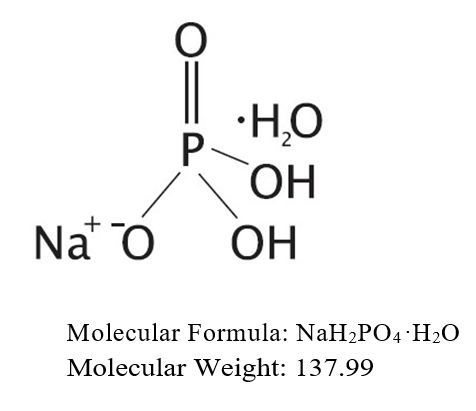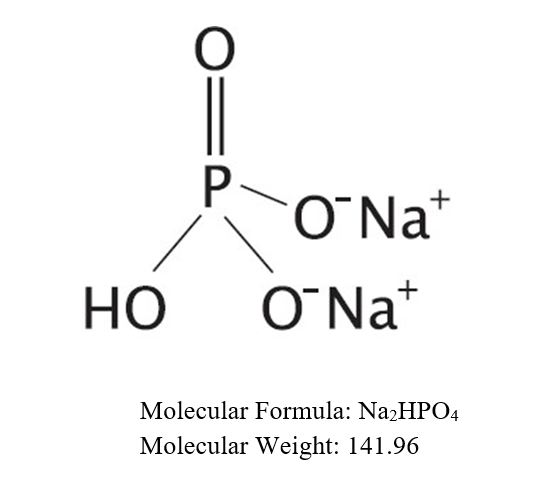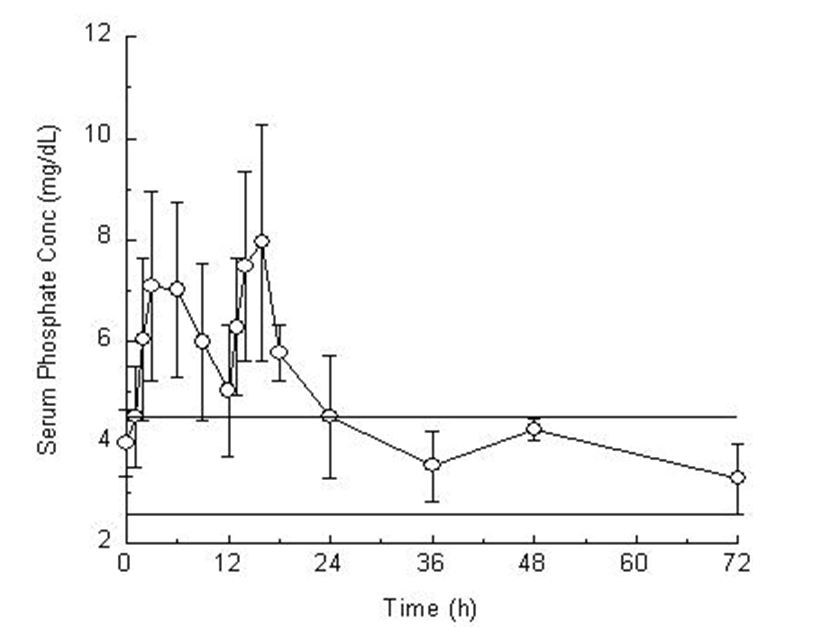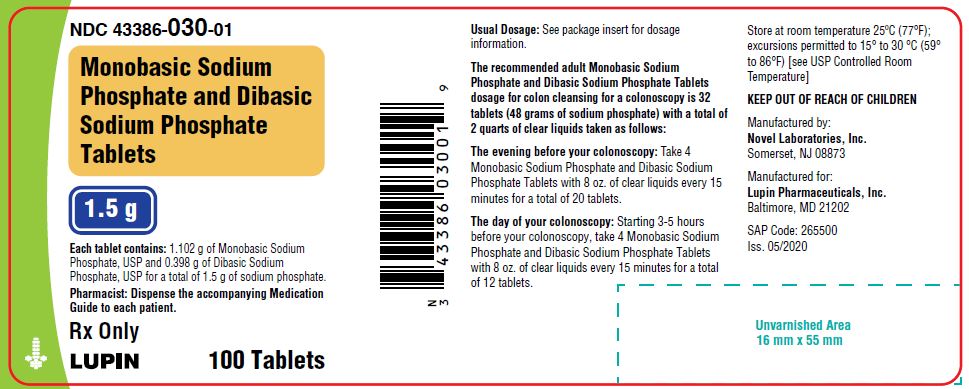 DRUG LABEL: Monobasic Sodium Phosphate and Dibasic Sodium Phosphate
NDC: 43386-030 | Form: TABLET
Manufacturer: Lupin Pharmaceuticals,Inc.
Category: prescription | Type: HUMAN PRESCRIPTION DRUG LABEL
Date: 20240130

ACTIVE INGREDIENTS: SODIUM PHOSPHATE, MONOBASIC, MONOHYDRATE 1.105 g/1 1; SODIUM PHOSPHATE, DIBASIC, ANHYDROUS 0.398 g/1 1
INACTIVE INGREDIENTS: MAGNESIUM STEARATE; POLYETHYLENE GLYCOL 8000

HIGHLIGHTS OF PRESCRIBING INFORMATION

These highlights do not include all the information needed to use MONOBASIC SODIUM PHOSPHATE AND DIBASIC SODIUM PHOSPHATE TABLETS safely and effectively. See full prescribing information for MONOBASIC SODIUM PHOSPHATE AND DIBASIC SODIUM PHOSPHATE TABLETS
Monobasic Sodium
Phosphate and Dibasic Sodium Phosphate Tablets, for oral use
Initial U.S. Approval:2006

RECENT MAJOR CHANGES

Warnings and Precautions (5.7) 11/2018

BOXED WARNING

WARNING: ACUTE PHOSPHATE NEPHROPATHY

See full prescribing information for complete boxed warning.

- Rare, serious reports of acute phosphate nephropathy in patients who received oral sodium phosphate products, including Monobasic Sodium Phosphate and Dibasic Sodium Phosphate Tablets, for colon cleansing prior to colonoscopy. Some cases have resulted in permanent impairment of renal function and some patients required long-term dialysis. (5.1)
- Patients at increased risk include those with increased age, hypovolemia, increased bowel transit time (such as bowel obstruction), active colitis, or baseline kidney disease, and those using medicines that affect renal perfusion or function (such as diuretics, angiotensin-converting enzyme [ACE] inhibitors, angiotensin receptor blockers [ARBs], and possibly nonsteroidal anti-inflammatory drugs [NSAIDs]). (5.1)
- Advise patients of the importance of following the recommended split dosage regimen and the importance of adequate hydration before, during and after the use of Monobasic Sodium Phosphate and Dibasic Sodium Phosphate Tablets. Avoid additional sodium phosphate-based products. (2.1,2.2)

1 INDICATIONS AND USAGE

Monobasic Sodium Phosphate and Dibasic Sodium Phosphate Tablets are an osmotic laxative indicated for cleansing of the colon as a preparation for colonoscopy in adults.

2 DOSAGE AND ADMINISTRATION

Important Administration Instructions:

- Two doses of Monobasic Sodium Phosphate and Dibasic Sodium Phosphate Tablets are required for a complete preparation for colonoscopy: the first dose the evening before the colonoscopy and the second dose on the morning of the colonoscopy. (2.1)
- Do not take other laxatives, particularly additional sodium phosphate- based purgative or enema products. (2.1,7.3)
- Do not take oral medications within 1 hour before or after starting each dose. (2.1 , 7.2)

Dosage Regimen (2.2)

The recommended adult dosage is 32 tablets taken orally with a total of 2 quarts of clear liquids in the following manner:

- Evening before colonoscopy: 4 tablets with 8 ounces of clear liquids every 15 minutes for a total of 20 tablets.
- Next morning: 4 tablets with 8 ounces of clear liquids every 15 minutes for a total of 12 tablets.

3 DOSAGE FORMS AND STRENGTHS

Tablets: 1.5 g of sodium phosphate (3)

4 CONTRAINDICATIONS

- Biopsy-proven acute phosphate nephropathy (4, 5.1)
- Gastrointestinal (GI) obstruction (4, 5.7)
- Gastric bypass or stapling surgery (4)
- Bowel perforation (4)
- Toxic colitis (4)
- Toxic megacolon (4)
- Hypersensitivity to sodium phosphate salts or any components of Monobasic Sodium Phosphate and Dibasic Sodium Phosphate Tablets (4, 5.7)

5 WARNINGS AND PRECAUTIONS

- Renal disease and electrolyte disorders : Use caution in severe renal impairment and those taking concurrent medications that increase risk, ensure adequate hydration, and consider laboratory assessments prior to and after use. (5.1, 7.1)
- Cardiac arrhythmias : Consider pre-dose and post-colonoscopy ECGs in patients at increased risk. (5.2)
- Seizures : Use caution in patients with a history of seizures and patients at increased risk of seizure, including medications that lower the seizure threshold. (5.3, 7.1)
- Suspected GI obstruction or perforation : Rule out diagnosis before administration. (4, 5.4)
- Colonic mucosal ulceration : Consider potential for mucosal ulcerations when interpreting colonoscopy findings in patients with known or suspected inflammatory bowel disease. Use with caution in patients with an acute exacerbation of chronic inflammatory bowel disease (5.5)
- Patients at risk for aspiration : Observe during administration. (5.6)
- Hypersensitivity reactions, including anaphylaxis : Inform patients to seek immediate medical care if symptoms occur. (5.7)

6 ADVERSE REACTIONS

Most common adverse reactions (≥3%) are: bloating, nausea, abdominal pain, and vomiting. (6.1)

To report SUSPECTED ADVERSE REACTIONS, contact Lupin Pharmaceuticals Inc. at 1-866-403-7592 or FDA at 1-800-FDA-1088 or www.fda.gov/medwatch.

7 DRUG INTERACTIONS

- Drugs that increase risks due to fluid and electrolyte changes. (7.1)

See 17 for PATIENT COUNSELING INFORMATION and Medication Guide.

FULL PRESCRIBING INFORMATION

BOXED WARNING

WARNING: ACUTE PHOSPHATE NEPHROPATHY

- There have been rare, but serious reports of acute phosphate nephropathy in patients who received oral sodium phosphate products, including Monobasic Sodium Phosphate and Dibasic Sodium Phosphate Tablets, for colon cleansing prior to colonoscopy. Some cases have resulted in permanent impairment of renal function and some patients required long-term dialysis [see Warnings and Precautions (5.1)] .
- While some cases have occurred in patients without identifiable risk factors, patients at increased risk of acute phosphate nephropathy may include those with increased age, hypovolemia, increased bowel transit time (such as bowel obstruction), active colitis, or baseline kidney disease, and those using medicines that affect renal perfusion or function (such as diuretics, angiotensin-converting enzyme [ACE] inhibitors, angiotensin receptor blockers [ARBs], and possibly nonsteroidal anti-inflammatory drugs [NSAIDs]) [see Warnings and Precautions (5.1)].
- Advise patients of the importance of following the recommended split dosage regimen and the importance of adequate hydration before, during and after the use of Monobasic Sodium Phosphate and Dibasic Sodium Phosphate Tablets. Avoid additional sodium phosphate- based purgative or enema products [see Dosage and Administration (2.1,2.2)] .

1 INDICATIONS AND USAGE

Monobasic Sodium Phosphate and Dibasic Sodium Phosphate Tablets are indicated for cleansing of the colon as a preparation for colonoscopy in adults.

2 DOSAGE AND ADMINISTRATION

2.1 Important Administration Instructions

- Correct fluid and electrolyte abnormalities before treatment with Monobasic Sodium Phosphate and Dibasic Sodium Phosphate Tablets[see Warnings and Precautions (5.1)] .
- Clear liquids must be consumed before, during and after taking Monobasic Sodium Phosphate and Dibasic Sodium Phosphate Tablets [see Dosage and Administration (2.1), Warnings and Precautions (5.1)] .
- Do not administer Monobasic Sodium Phosphate and Dibasic Sodium Phosphate Tablets within 7 days of a previous use.
- Two doses of Monobasic Sodium Phosphate and Dibasic Sodium Phosphate Tablets are required for a complete preparation for colonoscopy: the first dose the evening before the colonoscopy and the second dose on the morning of the colonoscopy [see Dosage and Administration (2.2)].
- Consume only clear liquids (no solid food) from the start of Monobasic Sodium Phosphate and Dibasic Sodium Phosphate Tablets treatment until after the colonoscopy.
- Do not eat or drink alcohol, milk, anything colored red or purple or any other foods containing pulp material.
- Do not take other laxatives while taking Monobasic Sodium Phosphate and Dibasic Sodium Phosphate Tablets, particularly additional sodium phosphate-based purgative or enema products [see Drug Interactions (7.3)] .
- Do not take oral medications within 1 hour before or after starting each dose of Monobasic Sodium Phosphate and Dibasic Sodium Phosphate Tablets[see Drug Interactions (7.2)] .

2.2 Dosage Regimen

Instruct adult patients that on the day before their colonoscopy, they can consume a light breakfast consisting of clear soup and/or plain yogurt (no solid foods) before noon, followed by only clear liquids until after the colonoscopy.

The recommended dose of Monobasic Sodium Phosphate and Dibasic Sodium Phosphate Tablets for colon cleansing for adult patients is 32 tablets (48 grams of sodium phosphate) taken orally with a total of 2 quarts of clear liquids in the following manner:

The evening before the colonoscopy: Take 4 Monobasic Sodium Phosphate and Dibasic Sodium Phosphate Tablets with 8 ounces of clear liquids every 15 minutes for a total of 20 tablets.

On the day of the colonoscopy starting 3 to 5 hours before the procedure: Take 4 Monobasic Sodium Phosphate and Dibasic Sodium Phosphate Tablets with 8 ounces of clear liquids every 15 minutes for a total of 12 tablets.

3 DOSAGE FORMS AND STRENGTHS

Monobasic Sodium Phosphate and Dibasic Sodium Phosphate Tablets are supplied as white to off-white uncoated tablet, modified oval shaped, biconvex, bisect on one side and plain on the other. Debossed "N" on the left side of the bisect and "03" on the right side of the bisect. Each Monobasic Sodium Phosphate and Dibasic Sodium Phosphate Tablets contains 1.102 grams of Monobasic Sodium Phosphate, USP and 0.398 grams of Dibasic Sodium Phosphate, USP for a total of 1.5 grams of sodium phosphate per tablet. Inert ingredients include polyethylene glycol 8000, NF; and magnesium stearate, NF.

4 CONTRAINDICATIONS

Monobasic Sodium Phosphate and Dibasic Sodium Phosphate Tablets are contraindicated in the following conditions:

- History of acute phosphate nephropathy [see Warnings and Precautions (5.1)]
- Gastrointestinal (GI) obstruction [see Warnings and Precautions (5.7)]
- Gastric bypass or stapling surgery
- Bowel perforation
- Toxic colitis
- Toxic megacolon
- Hypersensitivity to sodium phosphate salts or any component of Monobasic Sodium Phosphate and Dibasic Sodium Phosphate Tablets[see Warnings and Precautions (5.7)].

5 WARNINGS AND PRECAUTIONS

5.1 Renal Disease, Acute Phosphate Nephropathy, and Electrolyte Disorders

Renal Disease and Acute Phosphate Nephropathy

There have been rare, but serious, reports of renal failure, acute phosphate nephropathy, and nephrocalcinosis in patients who received oral sodium phosphate products, including Monobasic Sodium Phosphate and Dibasic Sodium Phosphate Tablets, for colon cleansing prior to colonoscopy. These cases often resulted in permanent impairment of renal function and several patients required long-term dialysis. The time to onset is typically within days; however, in some cases, the diagnosis of these events has been delayed up to several months after the ingestion of these products. Patients at increased risk of acute phosphate nephropathy may include patients with the following: hypovolemia, baseline kidney disease, increased age, and patients using medicines that affect renal perfusion or function [such as diuretics, angiotensin-converting enzyme (ACE) inhibitors, angiotensin receptor blockers, and possibly nonsteroidal anti-inflammatory drugs (NSAIDs) [see Drug Interactions (7.1)].

Electrolyte Disorders

Bowel preparations, including Monobasic Sodium Phosphate and Dibasic Sodium Phosphate Tabletscan cause fluid and electrolyte disturbances, which can lead to serious adverse reactions including cardiac arrhythmias, seizures and renal impairment [see Adverse Reactions (6.2)].

Patient Management

- Monobasic Sodium Phosphate and Dibasic Sodium Phosphate Tablets are contraindicated in patients with a history of acute phosphate nephropathy [see Contraindications (4)]. Use Monobasic Sodium Phosphate and Dibasic Sodium Phosphate Tablets with caution in patients with severe renal impairment (creatinine clearance less than 30 mL/minute), with conditions, or who are taking medications, that increase the risk for fluid and electrolyte disturbances or may increase the risk of arrhythmias, seizures, or renal impairment. Consider performing baseline and post-colonoscopy labs (phosphate, calcium, potassium, sodium, creatinine, and BUN) in these patients [see Drug Interactions (7.1)] .
- Correct electrolyte abnormalities such as hypernatremia, hyperphosphatemia, hypokalemia, or hypocalcemia before treatment with Monobasic Sodium Phosphate and Dibasic Sodium Phosphate Tablets[see Dosage and Administration (2.1)] .
- Avoid additional sodium phosphate-based purgative or enema products [see Drug Interactions (7.1)] .
- Advise all patients to hydrate adequately before, during, and after the use of Monobasic Sodium Phosphate and Dibasic Sodium Phosphate Tablets[see Dosage and Administration (2.1,2.2)] .
- If a patient develops significant vomiting or signs of dehydration while or after taking Monobasic Sodium Phosphate and Dibasic Sodium Phosphate Tablets, consider performing post-colonoscopy lab tests [electrolytes, creatinine, and blood urea nitrogen (BUN)].

5.2 Cardiac Arrhythmias

There have been rare reports of serious arrhythmias associated with the use of ionic osmotic laxative products for bowel preparation. QT prolongation with sodium phosphate tablets has been associated with electrolyte imbalances, such as hypokalemia and hypocalcemia.

Use caution when prescribing Monobasic Sodium Phosphate and Dibasic Sodium Phosphate Tablets for patients at increased risk of arrhythmias (e.g., patients with a history of prolonged QT, uncontrolled arrhythmias, recent myocardial infarction, unstable angina, congestive heart failure, or cardiomyopathy) and those taking medications known to prolong the QT interval, since serious complications may occur. Consider pre-dose and post-colonoscopy ECGs in patients at increased risk of serious cardiac arrhythmias.

5.3 Seizures

There have been rare reports of generalized tonic-clonic seizures and/or loss of consciousness associated with use of sodium phosphate osmotic laxative products, such as Monobasic Sodium Phosphate and Dibasic Sodium Phosphate Tablets, in patients with no prior history of seizures. The seizure cases were associated with electrolyte abnormalities (e.g., hyponatremia, hypokalemia, hypocalcemia, and hypomagnesemia) and low serum osmolality. The neurologic abnormalities resolved with correction of fluid and electrolyte abnormalities.

Use Monobasic Sodium Phosphate and Dibasic Sodium Phosphate Tablets with caution in patients with a history of seizures and in patients at higher risk of seizure, such as patients taking medications that lower the seizure threshold (such as tricyclic antidepressants), patients withdrawing from alcohol or benzodiazepines, or patients with known or suspected hyponatremia [see Drug Interactions (7.1)].

5.4 Use in Patients with Significant Gastrointestinal Disease

If gastrointestinal obstruction or perforation is suspected, perform appropriate diagnostic studies to rule out these conditions before administering Monobasic Sodium Phosphate and Dibasic Sodium Phosphate Tablets [see Contraindications (4)].

Use with caution in patients with severe active ulcerative colitis.

5.5 Colonic Mucosal Ulceration and Inflammatory Bowel Disease

Osmotic laxatives, including Monobasic Sodium Phosphate and Dibasic Sodium Phosphate Tablets, may induce colonic mucosal aphthous ulcerations. In the Monobasic Sodium Phosphate and Dibasic Sodium Phosphate Tablets clinical program, aphthous ulcers were observed in 3% of patients who took the recommended Monobasic Sodium Phosphate and Dibasic Sodium Phosphate Tablets dosing regimen.

Consider the potential for mucosal ulcerations resulting from bowel preparation when interpreting colonoscopic finding should in patients with known or suspected inflammatory bowel disease.

Use Monobasic Sodium Phosphate and Dibasic Sodium Phosphate Tablets with caution in patients experiencing an acute exacerbation of chronic inflammatory bowel disease as published data suggest that sodium phosphate absorption may be enhanced in such patients.

5.6 Aspiration

Patients with impaired gag reflex or other swallowing abnormalities are at risk for regurgitation or aspiration of Monobasic Sodium Phosphate and Dibasic Sodium Phosphate Tablets. Observed these patients during administration of Monobasic Sodium Phosphate and Dibasic Sodium Phosphate Tablets.

5.7 Hypersensitivity Reactions

Monobasic Sodium Phosphate and Dibasic Sodium Phosphate Tablets may cause serious hypersensitivity reactions including anaphylaxis, angioedema, rash, urticaria, and throat tightness [see Adverse Reactions (6.2)]. Inform patients of the signs and symptoms of anaphylaxis and instruct them to seek immediate medical care should signs and symptoms occur.

6 ADVERSE REACTIONS

The following serious or otherwise important adverse reactions for bowel preparations are described elsewhere in the labeling:

- Renal Disease, Acute Phosphate Nephropathy, and Electrolyte Disorders [see Warnings and Precautions (5.1)]
- Cardiac Arrhythmias [see Warnings and Precautions (5.2)]
- Seizures [see Warnings and Precautions (5.3)]
- Use in Patients with Significant Gastrointestinal Disease [see Warnings and Precautions (5.4)]
- Colonic Mucosal Ulceration and Inflammatory Bowel Disease [see Warnings and Precautions (5.5)]
- Aspiration [see Warnings and Precautions (5.6)]
- Hypersensitivity Reactions [see Warnings and Precautions (5.7)]

6.1 Clinical Trials Experience

Because clinical trials are conducted under widely varying conditions, adverse reaction rates observed in the clinical trials of a drug cannot be directly compared to rates in the clinical trials of another drug and may not reflect the rates observed in practice.

The safety of Monobasic Sodium Phosphate and Dibasic Sodium Phosphate Tablets was evaluated in two randomized, investigator-blinded, active controlled trials in 931 adult patients undergoing elective colonoscopy. The mean age of the study population was 60 years (range 20 to 89 years), 88% of patients were Caucasian and 55% were female [see Clinical Studies (14)].

Table 1 shows the most common adverse reactions reported in greater than 3% of patients by treatment group in Study 1 [see Clinical Studies (14)]. Since diarrhea was considered as a part of the efficacy of Monobasic Sodium Phosphate and Dibasic Sodium Phosphate Tablets, diarrhea was not defined as an adverse event in this clinical trial.

Table 1: Common Adverse Reactions^1 in Patients Undergoing Colonoscopy in Study 1
 | Monobasic Sodium Phosphate and Dibasic Sodium Phosphate Tablets 32 tabs (48 g) N=272 | Monobasic Sodium Phosphate and Dibasic Sodium Phosphate Tablets 40 tabs (60 g) N=265 | Sodium Phosphate2 40 tabs (60 g) N=268
Bloating | 31% | 39% | 41%
Nausea | 26% | 37% | 30%
Abdominal Pain | 23% | 24% | 25%
Vomiting | 4% | 10% | 9%
^1Reported in more than 3% of patients in at least one treatment group
^2Another oral formulation of monobasic sodium phosphate and dibasic sodium phosphate

Electrolyte Abnormalities in Study 1

Hyperphosphatemia

A total of, 96%, 96%, and 93% of patients who took 60 grams of oral sodium phosphate, 60 grams of Monobasic Sodium Phosphate and Dibasic Sodium Phosphate Tablets, and 48 grams of Monobasic Sodium Phosphate and Dibasic Sodium Phosphate Tablets, respectively, developed hyperphosphatemia (defined as phosphate level > 5.1 mg/dL) on the day of the colonoscopy. In this study, patients who took 60 grams of oral sodium phosphate, 60 grams of Monobasic Sodium Phosphate and Dibasic Sodium Phosphate Tablets, and 48 grams of Monobasic Sodium Phosphate and Dibasic Sodium Phosphate Tablets had baseline mean phosphate levels of 3.5, 3.5, and 3.6 mg/dL and subsequently developed mean phosphate levels of 7.6, 7.9, and 7.1 mg/dL, respectively, on the day of the colonoscopy.

Hyperkalemia

A total of 20%, 22%, and 18% of patients who took 60 grams of oral sodium phosphate, 60 grams of Monobasic Sodium Phosphate and Dibasic Sodium Phosphate Tablets, and 48 grams of Monobasic Sodium Phosphate and Dibasic Sodium Phosphate Tablets, respectively, developed hypokalemia (defined as a potassium level < 3.4 mEq/L) on the day of the colonoscopy. In this study, patients who took 60 grams of oral sodium phosphate, 60 grams of Monobasic Sodium Phosphate and Dibasic Sodium Phosphate Tablets, and 48 grams of Monobasic Sodium Phosphate and Dibasic Sodium Phosphate Tablets all had baseline potassium levels of about 4.3 mEq/L and then developed a mean potassium level of 3.7 mEq/L on the day of the colonoscopy.

Several patients on all three sodium phosphate regimens developed hypocalcemia and hypernatremia that did not require treatment.

The Monobasic Sodium Phosphate and Dibasic Sodium Phosphate Tablets 60-gram dosage regimen was associated with an increased risk of adverse reactions compared to the 48- gram dosage regimen and a similar overall response rate [see Clinical Studies (14)]. Therefore, the Monobasic Sodium Phosphate and Dibasic Sodium Phosphate Tablets 60-gram dosage is not a recommended regimen [see Dosage and Administration (2.2)].

6.2 Postmarketing Experience

The following adverse reactions have been identified during post-approval use of Monobasic Sodium Phosphate and Dibasic Sodium Phosphate Tablets. Because these reactions are reported voluntarily from a population of unknown size, it is not always possible to reliably estimate their frequency or establish a causal relationship to drug exposure.

Hypersensitivity reactions: anaphylaxis, angioedema (swelling of the lips, tongue and face), rash, pruritus, urticaria, throat tightness, bronchospasm, dyspnea, pharyngeal edema, dysphagia, and paresthesia.

Cardiovascular: Arrhythmias

Nervous system: Seizures

Renal: Renal impairment, increased blood urea nitrogen (BUN), increased creatinine, acute renal failure, acute phosphate nephropathy, nephrocalcinosis, and renal tubular necrosis.

7 DRUG INTERACTIONS

7.1 Drugs That May Increase Risks due to Fluid and Electrolyte Abnormalities

Use caution when prescribing Monobasic Sodium Phosphate and Dibasic Sodium Phosphate Tablets for patients with conditions, or who are using medications, that increase the risk for fluid and electrolyte disturbances or may increase the risk of renal impairment, seizures, arrhythmias, or prolonged QT in the setting of fluid and electrolyte abnormalities. Consider additional patient evaluations as appropriate in patients taking these concomitant medications [see Warnings and Precautions (5.1,5.2,5.3)].

7.2 Potential for Reduced Drug Absorption

Monobasic Sodium Phosphate and Dibasic Sodium Phosphate Tablets can reduce the absorption of other coadministered oral medications. Administer oral medications at least 1 hour before or 1 hour after starting each Monobasic Sodium Phosphate and Dibasic Sodium Phosphate Tablets dose [see Dosage and Administration (2.1)].

7.3 Other Sodium Phosphate-Based Laxatives

Administration of additional sodium phosphate-based purgative or enema products with Monobasic Sodium Phosphate and Dibasic Sodium Phosphate Tablets may increase the risk of acute phosphate nephropathy. Avoid concomitant use [see Warnings and Precautions (5.1)].

8 USE IN SPECIFIC POPULATIONS

8.1 Pregnancy

Risk Summary

There are no available data on sodium phosphate use in pregnant women to inform a drug-associated risk for adverse developmental outcomes.

Animal reproduction studies have not been conducted with sodium phosphate.

The estimated background risk of major birth defects and miscarriage for the indicated population is unknown. All pregnancies have a background risk of birth defect, loss, or other adverse outcomes. In the U.S. general population, the estimated background risk of major birth defects and miscarriage in clinically recognized pregnancies is 2% to 4% and 15% to 20%, respectively.

8.2 Lactation

Risk Summary

There are no data available to assess the presence of sodium phosphate in human milk, the effects of the drug on the breastfed infant, or the effects of the drug on milk production.

The lack of clinical data during lactation precludes a clear determination of the risk of Monobasic Sodium Phosphate and Dibasic Sodium Phosphate Tablets to a child during lactation; therefore, the developmental and health benefits of breastfeeding should be considered along with the mother's clinical need for Monobasic Sodium Phosphate and Dibasic Sodium Phosphate Tablets and any potential adverse effects on the breastfed child from Monobasic Sodium Phosphate and Dibasic Sodium Phosphate Tablets or from the underlying maternal condition.

8.4 Pediatric Use

Safety and effectiveness in pediatric patients have not been established.

8.5 Geriatric Use

Of the 599 patients in clinical trials receiving at least 48 grams of Monobasic Sodium Phosphate and Dibasic Sodium Phosphate Tablets, 134 (22%) were 65 years of age or older, while 27 (5%) were 75 years of age or older.

No overall differences in safety or effectiveness were observed between geriatric patients and younger patients. However, the mean phosphate levels in geriatric patients were greater than the phosphate levels in younger patients after Monobasic Sodium Phosphate and Dibasic Sodium Phosphate Tablets administration. The mean colonoscopy-day phosphate levels in patients 18-64, 65-74, and ≥ 75 years old who received the recommended Monobasic Sodium Phosphate and Dibasic Sodium Phosphate Tablets dosage regimen in Study 1were 7.0, 7.3, and 8.0 mg/dL, respectively. After Monobasic Sodium Phosphate and Dibasic Sodium Phosphate Tablets administration, the mean phosphate levels in patients 18-64, 65-74, and ≥ 75 years old were 7.4, 7.9, and 8.0 mg/dL, respectively. Greater sensitivity of some older individuals cannot be ruled out; therefore, use Monobasic Sodium Phosphate and Dibasic Sodium Phosphate Tablets with caution in geriatric patients. Advise geriatric patients to adequately hydrate before, during, and after the use of Monobasic Sodium Phosphate and Dibasic Sodium Phosphate Tablets.

Sodium phosphate is known to be substantially excreted by the kidney, and the risk of adverse reactions with sodium phosphate may be greater in patients with impaired renal function. Since geriatric patients are more likely to have impaired renal function, consider performing baseline and post-colonoscopy labs (phosphate, calcium, potassium, sodium, creatinine, and BUN) in these patients [see Warnings and Precautions (5.1)].

8.6 Renal Impairment

Sodium phosphate is substantially excreted by the kidney. Use Monobasic Sodium Phosphate and Dibasic Sodium Phosphate Tablets with caution in patients with severe renal impairment (creatinine clearance less than 30 mL/min) or patients taking concomitant medications that may affect renal function. These patients may be at risk for renal injury. Advise these patients of the importance of adequate hydration before, during and after the use of Monobasic Sodium Phosphate and Dibasic Sodium Phosphate Tablets, and consider performing baseline and post-colonoscopy labs (phosphate, calcium, potassium, sodium, creatinine, and BUN) in these patients [see Warnings and Precautions (5.1), Drug Interactions (7.1)].

10 OVERDOSAGE

Overdosage of Monobasic Sodium Phosphate and Dibasic Sodium Phosphate Tablets may lead to severe electrolyte disturbances, including hyperphosphatemia, hypocalcemia, hypernatremia, or hypokalemia, as well as dehydration and hypovolemia, with attendant signs and symptoms of these disturbances. Certain severe electrolyte disturbances resulting from overdose may lead to cardiac arrhythmias, seizure, renal failure, and death [see Warnings and Precautions (5.1, 5.2, 5.3)]. Monitor for fluid and electrolyte disturbances and treated symptomatically.

11 DESCRIPTION

Monobasic Sodium Phosphate and Dibasic Sodium Phosphate Tablets (sodium phosphate monobasic monohydrate and sodium phosphate dibasic anhydrous) is an osmotic laxative used to clean the colon prior to colonoscopy. Monobasic Sodium Phosphate and Dibasic Sodium Phosphate Tablets is manufactured with a highly soluble tablet binder and does not contain microcrystalline cellulose (MCC). Monobasic Sodium Phosphate and Dibasic Sodium Phosphate Tablets are white to off-white uncoated tablet, modified oval shaped, biconvex, bisect on one side and plain on the other. Debossed "N" on the left side of the bisect and "03" on the right side of the bisect. Each Monobasic Sodium Phosphate and Dibasic Sodium Phosphate Tablet contains 1.102 grams of Monobasic Sodium Phosphate, USP and 0.398 grams of Dibasic Sodium Phosphate, USP for a total of 1.5 grams of sodium phosphate per tablet. Inert ingredients include polyethylene glycol 8000, NF; and magnesium stearate, NF. Monobasic Sodium Phosphate and Dibasic Sodium Phosphate Tablets is gluten-free.

The structural and molecular formulae and molecular weights of the active ingredients are shown below:

- Monobasic sodium phosphate, USP

- Dibasic sodium phosphate, USP

12 CLINICAL PHARMACOLOGY

12.1 Mechanism of Action

The primary mode of action is the osmotic effect of sodium, which induces a laxative effect. The physiological consequence is increased water retention in the lumen of the colon, resulting in loose stools.

12.2 Pharmacodynamics

Administration of the recommended Monobasic Sodium Phosphate and Dibasic Sodium Phosphate Tablets dosage regimen has a purgative effect for approximately 1 to 3 hours.

12.3 Pharmacokinetics

Pharmacokinetic studies with Monobasic Sodium Phosphate and Dibasic Sodium Phosphate Tablets have not been conducted. However, the following pharmacokinetic study was conducted with another oral tablet formulation of sodium phosphate which contain the same active ingredients as Monobasic Sodium Phosphate and Dibasic Sodium Phosphate Tablets at a dose that is 25% greater than the Monobasic Sodium Phosphate and Dibasic Sodium Phosphate Tablets dose.

Absorption

An open-label pharmacokinetic study of oral sodium phosphate in healthy subjects was performed to determine the concentration-time profile of serum inorganic phosphorus levels after oral sodium phosphate administration. All subjects received the approved dosing regimen for colon cleansing of 60 grams of sodium phosphate with a total liquid volume of

3.6 quarts. A 30-gram dose (20 tablets given as 3 tablets every 15 minutes with 8 ounces of clear liquids) was given beginning at 6 PM in the evening. The 30-gram dose (20 tablets given as 3 tablets every 15 minutes with 8 ounces of clear liquids) was repeated the following morning beginning at 6 AM.

Twenty-three healthy subjects (mean age 57 years old; 57% male and 43% female; and 65% Hispanic, 30% Caucasian, and 4% African-American) participated in this pharmacokinetic study. The serum phosphorus level rose from a mean

(± standard deviation) baseline of 4.0 (± 0.7) mg/dL to 7.7 (± 1.6 mg/dL), at a median of 3 hours after the administration of the first 30-gram dose of sodium phosphate tablets (see Figure 1). The serum phosphorus level rose to a mean of 8.4 (± 1.9) mg/dL, at a median of 4 hours after the administration of the second 30-gram dose of sodium phosphate tablets. The serum phosphorus level remained above baseline for a median of 24 hours after the administration of the initial dose of sodium phosphate tablets (range 16 to 48 hours).

Figure 1. Mean (±Standard Deviation) Serum Phosphorus Concentrations

The upper (4.5 mg/dL) and lower (2.6 mg/dL) reference limits for serum phosphate are represented by solid bars.

Specific Populations

Male and Female Patients: No difference in serum phosphate AUC values were observed in the single pharmacokinetic study conducted with sodium phosphate tablets in 13 male and 10 female healthy subjects.

Elderly Patients: In a single pharmacokinetic study of sodium phosphate tablets, which included 6 elderly subjects, plasma half-life increased two-fold in subjects > 70 years of age compared to subjects < 50 years of age (3 subjects and 5 subjects, respectively) [see Use in Specific Populations (8.5)].

Patients with Renal Impairment: The effect of renal impairment on the pharmacokinetics of Monobasic Sodium Phosphate and Dibasic Sodium Phosphate Tablets has not been studied. The inorganic form of phosphate in the circulating plasma is excreted almost entirely by the kidneys [see Warnings and Precautions (5.1), Use in Specific Populations (8.6)].

14 CLINICAL STUDIES

The colon cleansing efficacy and safety of Monobasic Sodium Phosphate and Dibasic Sodium Phosphate Tablets was evaluated in a randomized, investigator-blinded, actively controlled, multicenter, U.S. trial in patients scheduled to have an elective colonoscopy (Study 1).

In Study 1, patients were randomized into one of the following three sodium phosphate treatment groups:

- An oral tablet formulation of sodium phosphate containing 60 grams of sodium phosphate given in split doses (30 grams in the evening before the colonoscopy and 30 grams on the next day) with at least 3.6 quarts of clear liquids;
- Monobasic Sodium Phosphate and Dibasic Sodium Phosphate Tablets containing 60 grams of sodium phosphate given in split doses (30 grams in the evening before the colonoscopy and 30 grams on the next day) with 2.5 quarts of clear liquids; and
- Monobasic Sodium Phosphate and Dibasic Sodium Phosphate Tablets containing 48 grams of sodium phosphate (30 grams in the evening before the colonoscopy and 18 grams on the next day) with 2 quarts of clear liquids.

Patients were instructed to eat a light breakfast before noon on the day prior to the colonoscopy and then were told to drink only clear liquids after noon on the day prior to the colonoscopy.

The primary efficacy endpoint was the overall colon cleansing response rate in the 4-point Colonic Contents Scale. Response was defined as a rating of "excellent" or "good" on the 4-point scale as determined by the blinded colonoscopist. This trial was designed to assess the non-inferiority of the two Monobasic Sodium Phosphate and Dibasic Sodium Phosphate Tablets groups compared to the active control group.

The efficacy analysis included 704 adult patients who had an elective colonoscopy. Patients ranged in age from 21 to 89 years old (mean age 56 years old) with 55% female and 45% male patients. Race was distributed as follows: 87% Caucasian, 10% African American, and 3% other race. The Monobasic Sodium Phosphate and Dibasic Sodium Phosphate Tablets 60-gram and 48-gram treatment groups demonstrated non-inferiority compared to the active control. See Table 2 for the results.

Table 2: Phase 3 Study – Overall Colon Content Cleansing Response Rates^1
Treatment Arm (grams of sodium phosphate) | No. of tablets taken at 6 PM on the day prior to colonoscopy | No. of tablets taken the next day^2 | Excellent | Good | Fair | Inadequate | Overall Response Rate (Excellent or Good)
Monobasic Sodium Phosphate and Dibasic Sodium Phosphate Tablets 32 tabs (48 g) n=236 | 20 | 12 | 76% | 19% | 3% | 2% | 95%
Monobasic Sodium Phosphate and Dibasic Sodium Phosphate Tablets 40 tabs (60 g) n=233 | 20 | 20 | 73% | 24% | 2% | 1% | 97%
Sodium Phosphate Tablets 40 tabs (60 g) n=235 | 20 | 20 | 51% | 43% | 6% | 0% | 94%
1Colon cleansing efficacy was based on response rate to treatment. A patient was considered to be a responder if overall colon cleansing was rated as "excellent" or "good" on a 4-point scale based on the amount of retained "colonic contents". Excellent was defined as >90% of mucosa seen, mostly liquid stool, minimal suctioning needed for adequate visualization. Good was defined as >90% of mucosa seen, mostly liquid stool, significant suctioning needed for adequate visualization. Fair was defined as >90% of mucosa seen, mixture of liquid and semisolid stool, could be suctioned and/or washed. Inadequate was defined as <90% of mucosa seen, mixture of semisolid and solid stool which could not be suctioned or washed.
2On the day of the colonoscopy, study medication was taken 3 to 5 hours before the start of the colonoscopy.

The Monobasic Sodium Phosphate and Dibasic Sodium Phosphate Tablets 60-gram dosage regimen had a similar overall response rate as the 48-gram dosage regimen and was associated with an increased risk of adverse reactions [see Adverse Reactions (6.1)]. Therefore, the Monobasic Sodium Phosphate and Dibasic Sodium Phosphate Tablets 60-gram dosage is not a recommended regimen [see Dosage and Administration (2.2)].

16 HOW SUPPLIED/STORAGE AND HANDLING

Monobasic Sodium Phosphate and Dibasic Sodium Phosphate Tablets are white to off-white uncoated tablet, modified oval shaped, biconvex, bisect on one side and plain on the other. Debossed "N" on the left side of the bisect and "03" on the right side of the bisect. Each Monobasic Sodium Phosphate and Dibasic Sodium Phosphate Tablet contains 1.102 grams of monobasic sodium phosphate, USP and 0.398 grams of dibasic sodium phosphate, USP for a total of 1.5 grams of sodium phosphate per tablet. Inert ingredients include polyethylene glycol 8000, NF; and magnesium stearate, NF.

Monobasic Sodium Phosphate and Dibasic Sodium Phosphate Tablets is packaged in a multi-dose, child-resistant bottle containing 100 tablets: NDC 43386-030-01.

Each bottle contains two silica desiccant packets, which should not be ingested.

Store at 25°C (77°F); excursions permitted to 15° to 30°C (59° to 86°F) [see USP Controlled Room Temperature]. Discard any unused portion.

17 PATIENT COUNSELING INFORMATION

Advise the patient to read the FDA-approved patient labeling (Medication Guide).

Instruct patients:

- On the importance of taking the recommended fluid regimen. Advise them to hydrate adequately with clear liquids before, during, and after the use of Monobasic Sodium Phosphate and Dibasic Sodium Phosphate Tablets [see Dosage and Administration (2.1), Warnings and Precautions (5.1)] . Examples of clear liquids can be found in the Medication Guide.
- Two doses of Monobasic Sodium Phosphate and Dibasic Sodium Phosphate Tablets are required for a complete preparation for colonoscopy.
- Do not eat or drink alcohol, milk, anything colored red or purple or any other foods containing pulp material.
- Not to take other laxatives or enemas made with sodium phosphate while they are taking Monobasic Sodium Phosphate and Dibasic Sodium Phosphate Tablets [see Drug Interactions (7.3)] .
- Not to take oral medications within one hour before or after starting each dose of Monobasic Sodium Phosphate and Dibasic Sodium Phosphate Tablets [see Drug Interactions (7.2)] .
- To contact their healthcare provider if they develop significant vomiting or signs of dehydration after taking Monobasic Sodium Phosphate and Dibasic Sodium Phosphate Tablets or if they experience cardiac arrhythmias or seizures [see Warnings and Precautions (5.1,5.2,5.3)].
- To seek immediate medical care should signs and symptoms of a hypersensitivity reaction occur [see Warnings and Precautions (5.7)] .

Manufactured by:

Novel Laboratories, Inc.

Somerset, NJ 08873

Manufactured for:

Lupin Pharmaceuticals Inc.

Baltimore, MD 21202

SAP Code: 265501

Iss. 05/2020

Medication Guide

Monobasic Sodium Phosphate and Dibasic Sodium Phosphate Tablets s

Read this Medication Guide before you start taking Monobasic Sodium Phosphate and Dibasic Sodium Phosphate Tablets. This information does not take the place of talking with your doctor about your medical condition or your treatment.

What is the most important information I should know about Monobasic Sodium Phosphate and Dibasic Sodium Phosphate Tablets?

Monobasic Sodium Phosphate and Dibasic Sodium Phosphate Tablets can cause serious side effects, including:

Serious kidney problems. Rare, but serious kidney problems can happen in people who take medicines made with sodium phosphate, including Monobasic Sodium Phosphate and Dibasic Sodium Phosphate Tablets, to clean the colon before colonoscopy. These kidney problems can sometimes lead to kidney failure or the need for dialysis for a long time. These problems often happen within a few days, but sometimes may happen several months after taking Monobasic Sodium Phosphate and Dibasic Sodium Phosphate Tablets.

Conditions that can make you more at risk for having serious kidney problems with Monobasic Sodium Phosphate and Dibasic Sodium Phosphate Tablets include if you:

- lose too much body fluid (dehydration)
- have slow moving bowels
- have a blockage in your intestine (bowel obstruction)
- have any disease that causes bowel inflammation (colitis)
- have kidney disease or kidney problems
- have heart failure
- take water pills, high blood pressure medicine, or nonsteroidal anti-inflammatory drugs (NSAIDs)

Increased age may increase your risk for having serious kidney problems with Monobasic Sodium Phosphate and Dibasic Sodium Phosphate Tablets.

Severe fluid loss (dehydration) and severe changes in body salts in the blood (electrolytes). People who take medicines to clean their colon before a colonoscopy, including Monobasic Sodium Phosphate and Dibasic Sodium Phosphate Tablets, can have severe loss of body fluid, with severe changes in body salts in the blood. These changes can be serious and can cause:

- abnormal heart rhythms
- kidney problems
- seizures. This can happen even if you have never had a seizure.

Tell your doctor if you have any of these symptoms of loss of too much body fluid (dehydration) while taking Monobasic Sodium Phosphate and Dibasic Sodium Phosphate Tablets:

- vomiting
- urinating less often than normal
- dizziness
- headache

See "What are the possible side effects of Monobasic Sodium Phosphate and Dibasic Sodium Phosphate Tablets?" for more information about side effects.

Important information about taking Monobasic Sodium Phosphate and Dibasic Sodium Phosphate Tablets:

- Two doses of Monobasic Sodium Phosphate and Dibasic Sodium Phosphate Tablets are needed to completely prepare for your colonoscopy. Take your first dose of Monobasic Sodium Phosphate and Dibasic Sodium Phosphate Tablets on the evening before your colonoscopy. Take your second dose of Monobasic Sodium Phosphate and Dibasic Sodium Phosphate Tablets on the morning of your colonoscopy.
- Drink plenty of clear liquids before, during, and after taking Monobasic Sodium Phosphate and Dibasic Sodium Phosphate Tablets.
- Do not take another laxative or enema that contains sodium phosphate while taking Monobasic Sodium Phosphate and Dibasic Sodium Phosphate Tablets. See "How should I take Monobasic Sodium Phosphate and Dibasic Sodium Phosphate Tablets?" for more information about how to take Monobasic Sodium Phosphate and Dibasic Sodium Phosphate Tablets.

What is Monobasic Sodium Phosphate and Dibasic Sodium Phosphate Tablets?

Monobasic Sodium Phosphate and Dibasic Sodium Phosphate Tablets is a prescription medicine used in adults to clean your colon before a colonoscopy. Monobasic Sodium Phosphate and Dibasic Sodium Phosphate Tablets cleans your colon by causing you to have diarrhea. Cleaning your colon helps your doctor see the inside of your colon more clearly during the colonoscopy.

It is not known if Monobasic Sodium Phosphate and Dibasic Sodium Phosphate Tablets are safe and effective in children.

Who should not take Monobasic Sodium Phosphate and Dibasic Sodium Phosphate Tablets?

Do not take Monobasic Sodium Phosphate and Dibasic Sodium Phosphate Tablets if you:

- have had a kidney biopsy that shows you have kidney problems because of too much phosphate.
- have stomach or bowel (intestine) blockage.
- had stomach surgery involving stapling or bypass.
- have an opening in the wall of your intestine (bowel perforation).
- have a severely inflamed colon (toxic colitis).
- have a very dilated intestine (toxic megacolon).
- are allergic to sodium phosphate salts or any of the ingredients in Monobasic Sodium Phosphate and Dibasic Sodium Phosphate Tablets. See the end of this Medication Guide for a complete list of ingredients in Monobasic Sodium Phosphate and Dibasic Sodium Phosphate Tablets.

What should I tell my doctor before taking Monobasic Sodium Phosphate and Dibasic Sodium Phosphate Tablets?

Before you take Monobasic Sodium Phosphate and Dibasic Sodium Phosphate Tablets, tell your doctor about all of your medical conditions, including if you:

- have problems with serious loss of body fluid (dehydration) and changes in blood salts (electrolytes).
- have kidney problems.
- have heart problems.
- have a history of seizures.
- have had stomach surgery.
- have stomach or bowel problems.
- have ulcerative colitis.
- have problems with swallowing, gastric reflux, or if you inhale food or fluid into your lungs when eating or drinking (aspirate).
- are withdrawing from alcohol use.
- are withdrawing from the use of a type of medicine called a benzodiazepine.
- are on a low salt diet.
- are pregnant or plan to become pregnant. It is not known if Monobasic Sodium Phosphate and Dibasic Sodium Phosphate Tablets will harm your unborn baby. Talk to your doctor if you are pregnant or plan to become pregnant.
- are breastfeeding or plan to breastfeed. It is not known if Monobasic Sodium Phosphate and Dibasic Sodium Phosphate Tablets passes into your breast milk. You and your doctor should decide if you will take Monobasic Sodium Phosphate and Dibasic Sodium Phosphate Tablets while breastfeeding.

Tell your doctor about all the medicines you take, including prescription and over-the-counter medicines, vitamins, and herbal supplements.

Monobasic Sodium Phosphate and Dibasic Sodium Phosphate Tablets may affect how other medicines work. Do not take medicines by mouth within 1 hour of starting each dose of Monobasic Sodium Phosphate and Dibasic Sodium Phosphate Tablets or 1 hour after you start taking each dose of Monobasic Sodium Phosphate and Dibasic Sodium Phosphate Tablets.

Especially tell your doctor if you take:

- water pills (diuretics).
- medicines for blood pressure or heart problems.
- medicines for kidney problems.
- medicines for pain, such as aspirin or a nonsteroidal anti-inflammatory drug (NSAID).
- medicine for seizures.
- a laxative for constipation. Do not take other laxatives while taking Monobasic Sodium Phosphate and Dibasic Sodium Phosphate Tablets, especially a laxative or enema that contains sodium phosphate.
- medicine for depression or other mental health problem called a benzodiazepine.

Ask your doctor or pharmacist if you are not sure if you take any of the medicines listed above.

Know the medicines you take. Keep a list of your medicines to show your doctor or pharmacist when you get a new prescription.

How should I take Monobasic Sodium Phosphate and Dibasic Sodium Phosphate Tablets?

- Take Monobasic Sodium Phosphate and Dibasic Sodium Phosphate Tablets exactly as prescribed by your doctor.
- On the day before your colonoscopy , you can eat a light breakfast before 12:00 PM (noon). Examples of foods that you can eat include: clear liquids and plain yogurt. Do not eat any solid foods on the day before your colonoscopy. After your light breakfast, eat or drink only clear liquids until after your colonoscopy.
- It is important for you to drink plenty of clear liquids before, during, and after taking Monobasic Sodium Phosphate and Dibasic Sodium Phosphate Tablets. This may help prevent kidney damage. Examples of clear liquids are:
- water
- clear soda
- clear broth soups
- gelatin (without added fruit or topping)
- herbal tea, black tea or coffee
- popsicles (without pieces of fruit or fruit pulp)
- watered down (diluted) (from concentrate) clear white grape juice
- strained limeade or lemonade fruit juices (without pulp) including apple juice or
- Eat or drink only clear liquids after 12:00 PM (noon) on the day before your colonoscopy until after your colonoscopy.
- Do not eat solid food starting on the day before your colonoscopy until after your colonoscopy.
- Do not eat or drink alcohol, milk, anything colored red or purple or any foods that have pulp.

You must read, understand, and follow these instructions to take Monobasic Sodium Phosphate and Dibasic Sodium Phosphate Tablets the right way:

On the evening before your colonoscopy, take a total of 20 Monobasic Sodium Phosphate and Dibasic Sodium Phosphate Tablets, as follows: Step 1. Take 4 Monobasic Sodium Phosphate and Dibasic Sodium Phosphate Tablets with 8 ounces of clear liquids.

Step 2. Wait 15 minutes.

Step 3. Take 4 more Monobasic Sodium Phosphate and Dibasic Sodium Phosphate Tablets with 8 ounces of clear liquids.

Step 4. Repeat Steps 2 and 3 above, three more times. Make sure you wait 15 minutes after each time.

On the day of your colonoscopy, take a total of 12 Monobasic Sodium Phosphate and Dibasic Sodium Phosphate Tablets starting about 3 to 5 hours before your colonoscopy, as follows:

Step 1. Take 4 Monobasic Sodium Phosphate and Dibasic Sodium Phosphate Tablets with 8 ounces of clear liquids.

Step 2. Wait 15 minutes

Step 3. Take 4 more Monobasic Sodium Phosphate and Dibasic Sodium Phosphate Tablets with 8 ounces of clear liquids.

Step 4. Repeat Steps 2 and 3 one more time.

If you take too much Monobasic Sodium Phosphate and Dibasic Sodium Phosphate Tablets, call your doctor or get medical help right away.

What should I avoid while taking Monobasic Sodium Phosphate and Dibasic Sodium Phosphate Tablets?

- Do not take other laxatives or enemas made with sodium phosphate while taking Monobasic Sodium Phosphate and Dibasic Sodium Phosphate Tablets.
- Do not use Monobasic Sodium Phosphate and Dibasic Sodium Phosphate Tablets if you have already used it in the last 7 days.

What are the possible side effects of Monobasic Sodium Phosphate and Dibasic Sodium Phosphate Tablets?

Monobasic Sodium Phosphate and Dibasic Sodium Phosphate Tablets can cause serious side effects, including:

- See "What is the most important information I should know about Monobasic Sodium Phosphate and Dibasic Sodium Phosphate Tablets?"
- Changes in certain blood tests. Your doctor may do blood tests before and after you take Monobasic Sodium Phosphate and Dibasic Sodium Phosphate Tablets to check your levels of calcium, phosphate, potassium, and sodium in your blood. Tell your doctor if you have any symptoms of too much fluid loss, including:
- vomiting o urinating less often than normal
- dizziness o headache
- Abnormal heartbeat (arrhythmias). Tell your doctor if you have an abnormal or irregular heartbeat while taking Monobasic Sodium Phosphate and Dibasic Sodium Phosphate Tablets.
- Seizures or fainting (loss of consciousness). People who take a medicine that contains sodium phosphate, such as Monobasic Sodium Phosphate and Dibasic Sodium Phosphate Tablets, can have seizures or faint even if they have not had seizures before. Tell your doctor right away if you have a seizure or faint while taking Monobasic Sodium Phosphate and Dibasic Sodium Phosphate Tablets.
- Sores (ulcers) in the lining of the colon. Tell your doctor right away if you have severe stomach-area (abdomen) pain or rectal bleeding.
- Serious allergic reaction. Get emergency medical care right away if you have symptoms of a serious allergic reaction, including:
- swelling of the face, lips, tongue or throat o dizziness or lightheadedness
- problems breathing or wheezing o skin rash
- throat tightness o raised red patches on your skin (hives)
- fainting
- The most common side effects of Monobasic Sodium Phosphate and Dibasic Sodium Phosphate Tablets are:
- bloating stomach (abdominal) pain
- nausea vomiting

Tell your doctor if you have any side effect that bothers you or that does not go away.

These are not all the possible side effects of Monobasic Sodium Phosphate and Dibasic Sodium Phosphate Tablets. For more information, ask your doctor or pharmacist. Call your doctor for medical advice about side effects. You may report side effects to FDA at 1-800-FDA-1088.

How should I store Monobasic Sodium Phosphate and Dibasic Sodium Phosphate Tablets?

- Store Monobasic Sodium Phosphate and Dibasic Sodium Phosphate Tablets at room temperature, between 68° F to 77° F (20° C to 25° C).
- Throw away any Monobasic Sodium Phosphate and Dibasic Sodium Phosphate Tablets that is not needed.

Keep Monobasic Sodium Phosphate and Dibasic Sodium Phosphate Tablets and all medicines out of the reach of children.

General information about the safe and effective use of Monobasic Sodium Phosphate and Dibasic Sodium Phosphate Tablets.

Medicines are sometimes prescribed for purposes other than those listed in a Medication Guide. Do not use Monobasic Sodium Phosphate and Dibasic Sodium Phosphate Tablets for a condition for which it was not prescribed. Do not give Monobasic Sodium Phosphate and Dibasic Sodium Phosphate Tablets to other people, even if they are going to have the same procedure that you are. It may harm them. You can ask your doctor or pharmacist for information that is written for health professionals.

What are the ingredients in Monobasic Sodium Phosphate and Dibasic Sodium Phosphate Tablets?

Active ingredients: monobasic sodium phosphate and dibasic sodium phosphate

Inactive ingredients: polyethylene glycol 8000 and magnesium stearate.

Monobasic Sodium Phosphate and Dibasic Sodium Phosphate Tablets is gluten-free.

This Medication Guide has been approved by the U.S. Food and Drug Administration.

Manufactured by:

Novel Laboratories, Inc.

Somerset, NJ 08873

Manufactured for:

Lupin Pharmaceuticals Inc.

Baltimore, MD 21202

SAP Code: 265501

Iss. 05/2020